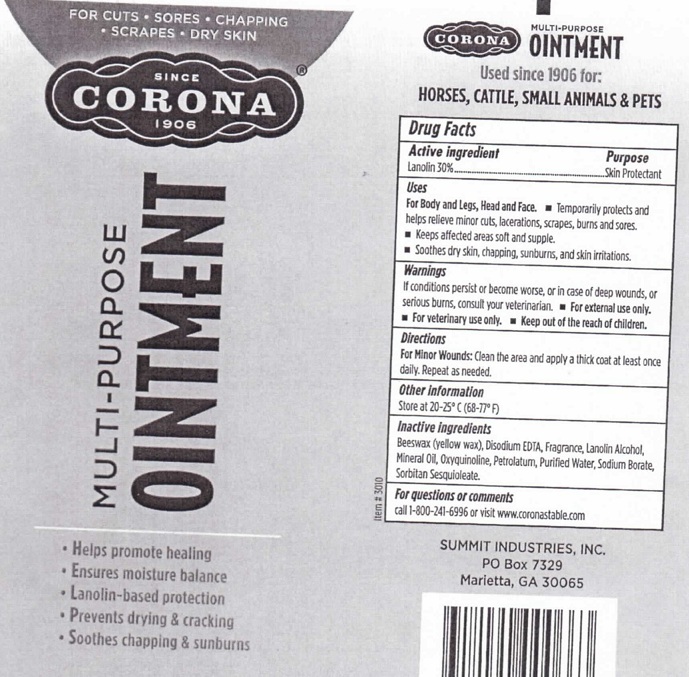 DRUG LABEL: CORONA MULTI-PURPOSE
                        
NDC: 12090-0029 | Form: OINTMENT
Manufacturer: SUMMIT INDUSTRIES
Category: animal | Type: OTC ANIMAL DRUG LABEL
Date: 20110511

ACTIVE INGREDIENTS: LANOLIN 30 g/100 g
INACTIVE INGREDIENTS: YELLOW WAX; EDETATE DISODIUM; LANOLIN ALCOHOLS; MINERAL OIL; OXYQUINOLINE; PETROLATUM; WATER; SODIUM BORATE; SORBITAN SESQUIOLEATE

CORONA MULTI-PURPOSE OINTMENT

Drug Facts

Active Ingredient Purpose

Lanolin 30% Skin protectant

Purpose - Skin protectant

Uses
For Body and Legs, Head and Face

Temporarily protects and helps relieve minor cuts, lacerations, scrapes, burns and sores.

Keeps affected areas soft and supple

Soothes dry skin, chapping, sunburns, and skin irritations.

Warnings

If conditions persist or become worse, or in case of deep wounds, or serious burns, consult y our veterinarian

For external use only

for veterinary use only

Keep out of reach of children

Directions:

For minor wounds: Clean the area and apply a thick coat at least once daily. Repeat as needed

Other Information

Store at 20 - 25 degrees C (68-77 degrees F)

Inactive Ingredients

Beeswax (yellow wax), Disodium EDTA, Fragrance, Lanolin Alcohol, Mineral Oil, Oxyquinoline, Petralatum, Purified Water, Sodium Borate, Sorbitan Sesquioleate.

For questions or comments

call 1-800-241-6996 or visit www.coronastable.com

PACKAGE LABEL

FOR CUTS SORES CHAPPING

SCRAPES DRY SKIN

SINCE 1096

CORONA

MULTI-PURPOSE OINTMENT

Helps promote healing

Ensures moisture balance

Lanolin-based protection

Prevents drying and cracking

Soothes chapping and sunburns

CORONA MULTIPURPOSE OINTMENT

Used since 1906 for:

Horses, Cattle, Small Animals, and Pets

SUMMIT INDUSTRIES, INC.

P.O. BOX 7329

Marietta, GA 30065